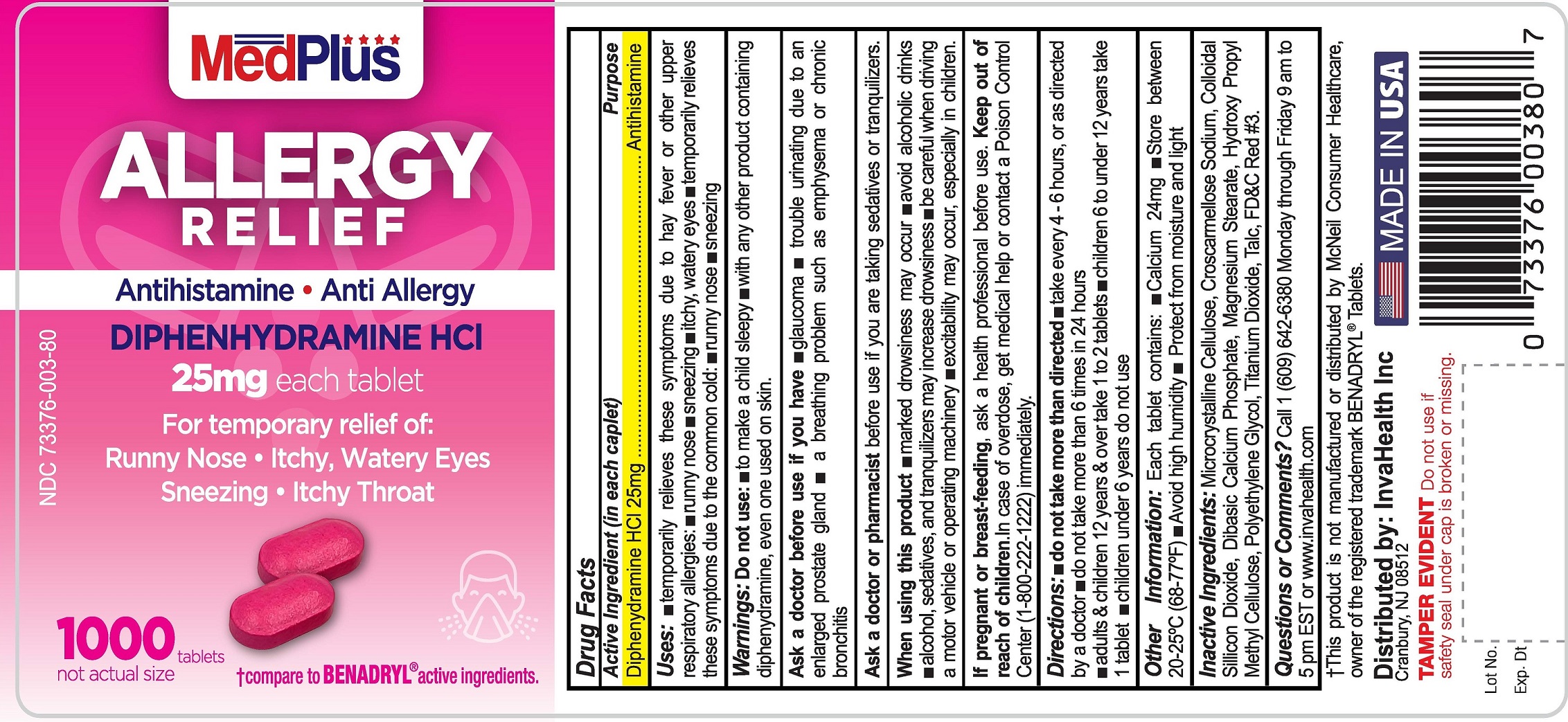 DRUG LABEL: Diphenhydramine HCl
NDC: 73376-003 | Form: TABLET, FILM COATED
Manufacturer: INVAHEALTH INC
Category: otc | Type: HUMAN OTC DRUG LABEL
Date: 20240108

ACTIVE INGREDIENTS: DIPHENHYDRAMINE HYDROCHLORIDE 25 mg/25 mg
INACTIVE INGREDIENTS: CROSCARMELLOSE SODIUM; FD&C RED NO. 3; TALC; POLYVINYL ALCOHOL, UNSPECIFIED; SILICON DIOXIDE; ANHYDROUS DIBASIC CALCIUM PHOSPHATE; MAGNESIUM STEARATE; MICROCRYSTALLINE CELLULOSE; POLYETHYLENE GLYCOL, UNSPECIFIED; TITANIUM DIOXIDE

ACTIVE INGREDIENT

Diphenhydramine HCl 25 mg

PURPOSE

Antihistamine

Do not use • to make a child sleepy • with any other product containing diphenhydramine, even one used on skin

ASK DOCTOR

a breathing problem such as emphysema or chronic bronchitis • glaucoma • trouble urinating due to an enlarged prostate gland

ASK DOCTOR/PHARMACIST

taking sedatives or tranquilizers

PREGNANCY OR BREAST FEEDING

ask a health professional before use.

KEEP OUT OF REACH OF CHILDREN

In case of overdose, get medical help or contact a Poison Control Center right away. (1-800-222-1222)

QUESTIONS

609-642-6380

INACTIVE INGREDIENT

Colloidal silicon dioxide, croscarmellose sodium, dicalcium phosphate, D&C Red No. 3, magnesium stearate, microcrystalline cellulose, polyethylene glycol, hydroxy propyl methyl cellulose talc, titanium dioxide

DOSAGE AND ADMINISTRATION

take every 4 to 6 hours do not take more than 6 doses in 24 hours

adults & children 12 years & over 1 to 2 tablets
children 6 to under 12 years 1 tablet
children under 6 years do not use this product in children under 6 years of age

Do not use

to make a child sleepy
with any other product containing diphenhydramine, even one used on skin

INDICATIONS AND USAGE

temporarily relieves these symptoms due to hay fever or other upper respiratory allergies:
runny nose
sneezing
itchy, watery eyes
itching of the nose or throat
temporarily relieves these symptoms due to the common cold:
runny nose
sneezing